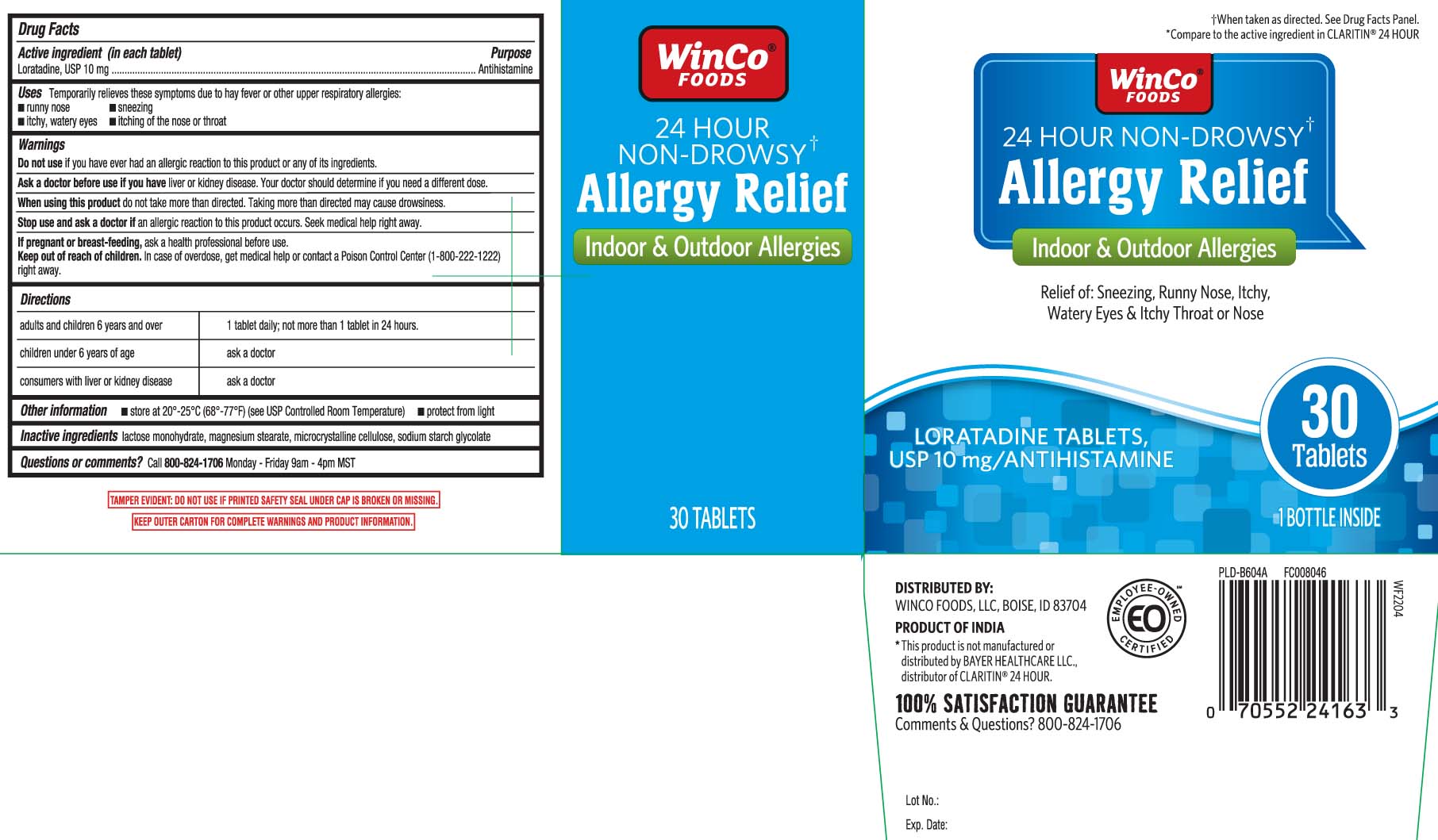 DRUG LABEL: Allergy Relief
NDC: 67091-350 | Form: TABLET
Manufacturer: WinCo Foods, LLC
Category: otc | Type: HUMAN OTC DRUG LABEL
Date: 20250408

ACTIVE INGREDIENTS: LORATADINE 10 mg/1 1
INACTIVE INGREDIENTS: LACTOSE MONOHYDRATE; MAGNESIUM STEARATE; MICROCRYSTALLINE CELLULOSE; SODIUM STARCH GLYCOLATE TYPE A CORN

Drug Facts

Active ingredient (in each tablet)

Loratadine, USP 10 mg

Purpose

Antihistamine

Uses

temporarily relieves these symptoms due to hay fever or other upper respiratory allergies:

- runny nose
- sneezing
- itchy, watery eyes
- itching of the nose or throat

Warnings

Do not use

if you have ever had an allergic reaction to this product or any of its ingredients.

Ask a doctor before use if you have

liver or kidney disease. Your doctor should determine if you need a different dose.

When using this product

do not take more than directed. Taking more than directed may cause drowsiness.

Stop use and ask a doctor if

an allergic reaction to this product occurs. Seek medical help right away.

If pregnant or breast-feeding,

ask a health professional before use.

Keep out of reach of children.

In case of overdose, get medical help or contact a Poison Control Center (1-800-222-1222) right away.

Directions

adults and children 6 years and over | 1 tablet daily; not more than 1 tablet in 24 hours
children under 6 years of age | ask a doctor
consumers with liver or kidney disease | ask a doctor

Other information

- store at 20º-25ºC (68º-77ºF) (see UPS Controlled Room Temperature)
- protect from light

Inactive ingredients

lactose monohydrate, magnesium stearate, microcrystalline cellulose, sodium starch glycolate

Questions or comments?

Call 1-800-824-1706 Monday-Friday 9AM-4PM MST

Principal Display Panel

†When taken as directed. See Drugs Facts Panel.

*Compare to the active ingredient in CLARITIN® 24 HOUR

24 HOUR NON-DROWSY†

Allergy Relief

Indoor & Outdoor Allergies

Original Prescription Strength

Relief of: Sneezing, Runny Nose, Itchy, Watery Eyes & Itchy Throat or Nose

LORATADINE TABLETS,

USP 10 mg / ANTIHISTAMINE

Tablets

*This product is not manufactured or distributed by BAYER HEALTHCARE LLC, distributor of CLARITIN®. 24 HOUR.

TAMPER EVIDENT: DO NOT USE IF PRINTED SAFETY SEAL UNDER CAP IS BROKEN OR MISSING.

KEEP OUTER CARTON FOR COMPLETE WARNINGS AND PRODUCT INFORMATION

DISTRIBUTED BY:

WINCO FOODS, LLC, BOISE, IS 83704

Package Label

WINCO FOODS 24 Hour Non-Drowsy Allergy Relief